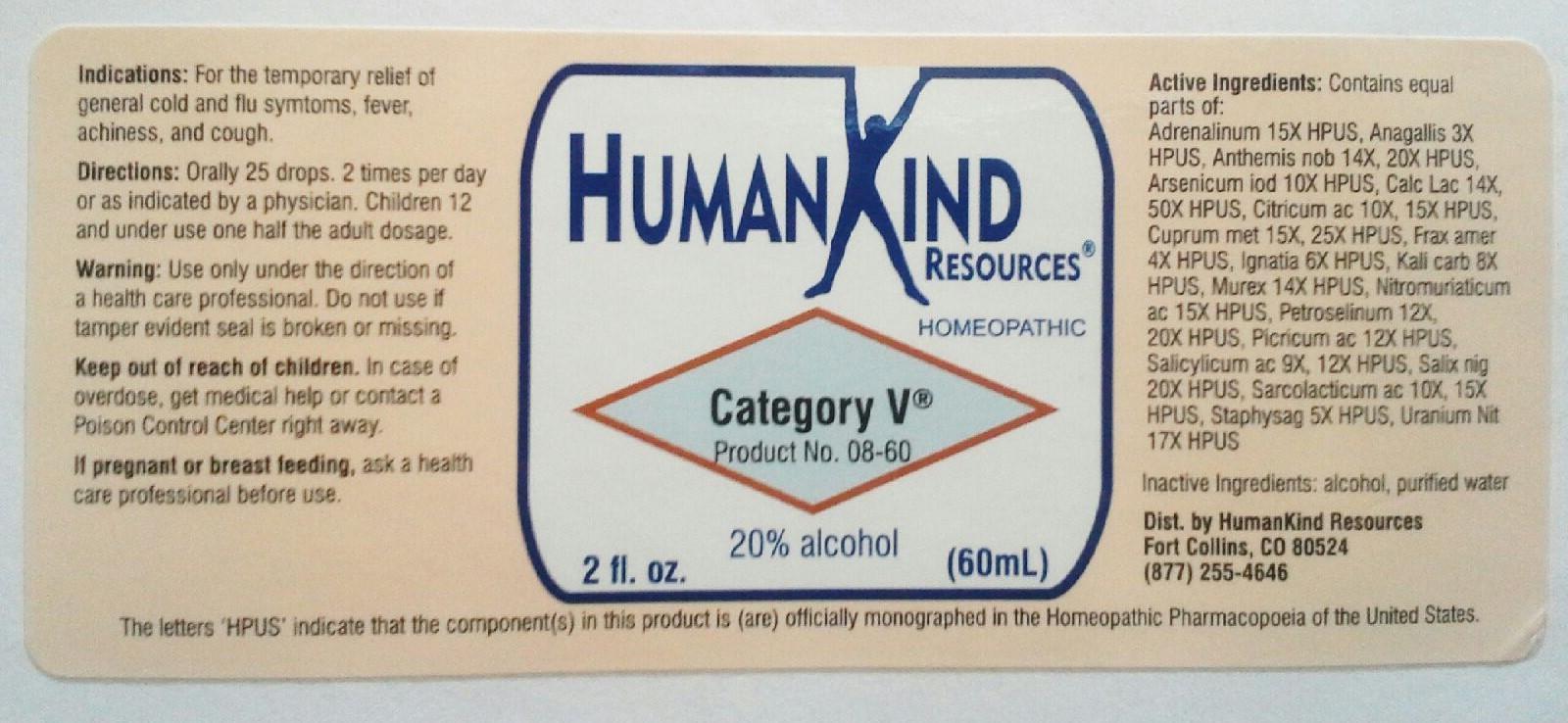 DRUG LABEL: Category V
NDC: 64616-086 | Form: LIQUID
Manufacturer: Vitality Works, Inc,
Category: homeopathic | Type: HUMAN OTC DRUG LABEL
Date: 20251217

ACTIVE INGREDIENTS: PICRIC ACID 12 [hp_X]/1 mL; PETROSELINUM CRISPUM 20 [hp_X]/1 mL; SALICYLIC ACID 12 [hp_X]/1 mL; SALIX NIGRA BARK 20 [hp_X]/1 mL; LACTIC ACID 15 [hp_X]/1 mL; DELPHINIUM STAPHISAGRIA SEED 5 [hp_X]/1 mL; URANYL NITRATE HEXAHYDRATE 17 [hp_X]/1 mL; HEXAPLEX TRUNCULUS HYPOBRANCHIAL GLAND JUICE 14 [hp_X]/1 mL; AQUA REGIA 15 [hp_X]/1 mL; COPPER 25 [hp_X]/1 mL; FRAXINUS AMERICANA BARK 4 [hp_X]/1 mL; EPINEPHRINE 15 [hp_X]/1 mL; ANAGALLIS ARVENSIS 3 [hp_X]/1 mL; CHAMAEMELUM NOBILE 20 [hp_X]/1 mL; ARSENIC TRIIODIDE 10 [hp_X]/1 mL; CALCIUM LACTATE 50 [hp_X]/1 mL; ANHYDROUS CITRIC ACID 15 [hp_X]/1 mL; STRYCHNOS IGNATII SEED 4 [hp_X]/1 mL; POTASSIUM CARBONATE 8 [hp_X]/1 mL
INACTIVE INGREDIENTS: ALCOHOL; WATER

Category V

Category V

Adrenalinum 15X Fraxinus Americana 4X Salicylicum Acidum 9X, 12X

Anagallis Arvensis 3X Ignatia Amara 6X Salix Nigra 20X

Anthemis Nobilis 10X Kali Carbonicum 8X Sarcolacticum Acidum 10X, 15X

Arsenicum Iodatum 10X Murex Purpurea 14X Staphysagria 5X

Calcerea Lactica 14X, 50X Nitromuriaticum Acidum 15X Uranium Nitricum 17X

Citricum Acidum 10X, 15X Petroselinum Sativum 12X, 20X

Cuprum Metallicum 15X, 25X Picricum Acidum 12X

Category V

Alcohol, Purified Water

Category V

Use only under the direction of a health care professional. Do not use if tamper evident seal is broken or missing.

Category V

Keep out of reach of children. In case of overdose, get medical help or contact a Poison Control Center right away.

Category V

For the temporary relief of general cold and flu symptoms, fever, achiness, and cough.

Category V

Orally 25 drops, 2 times per day or as directed by a physician. Children 12 and under use one half the adult dosage.

Category V

Eases cold and flu symptoms, fever, achiness and cough.